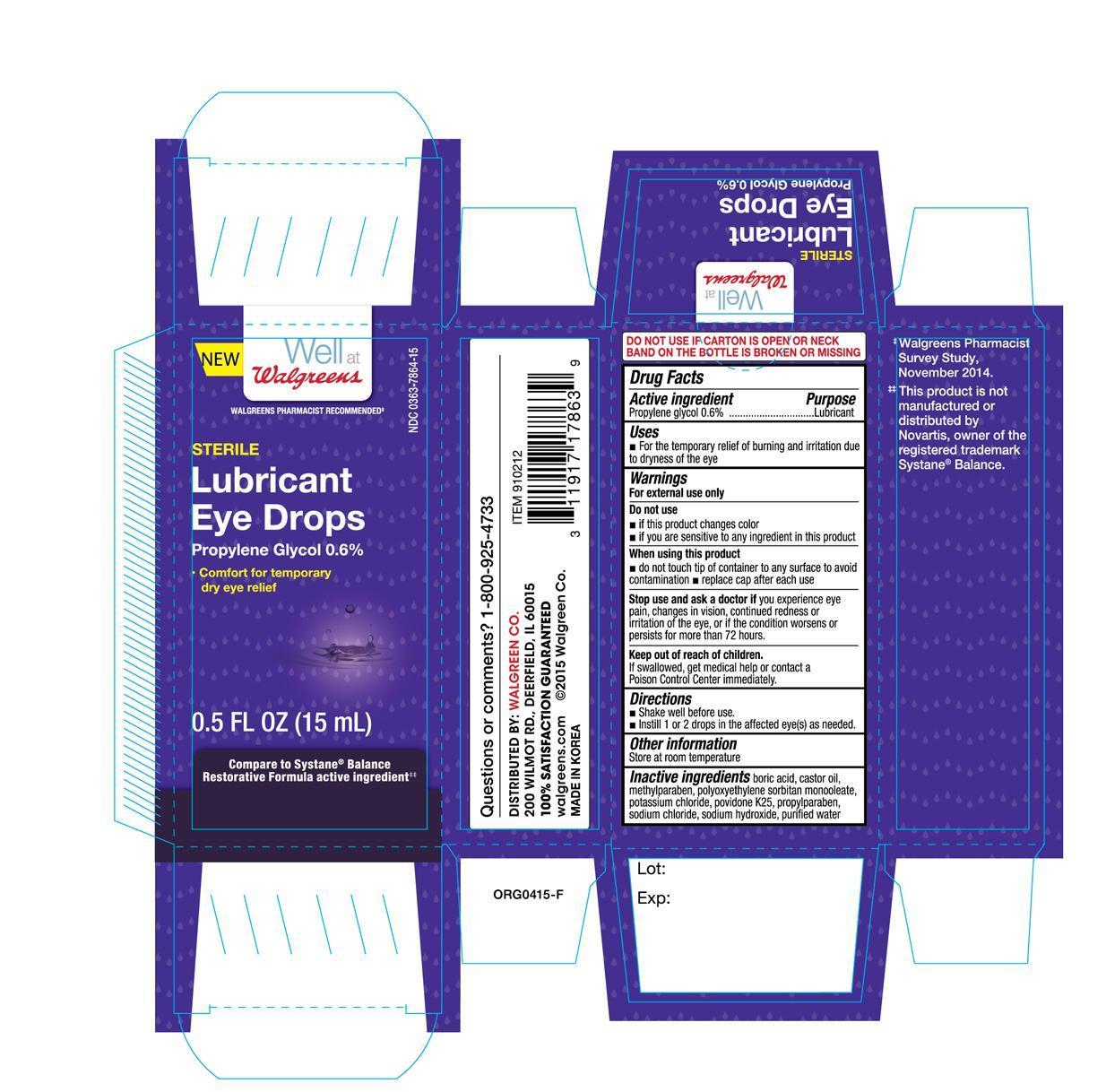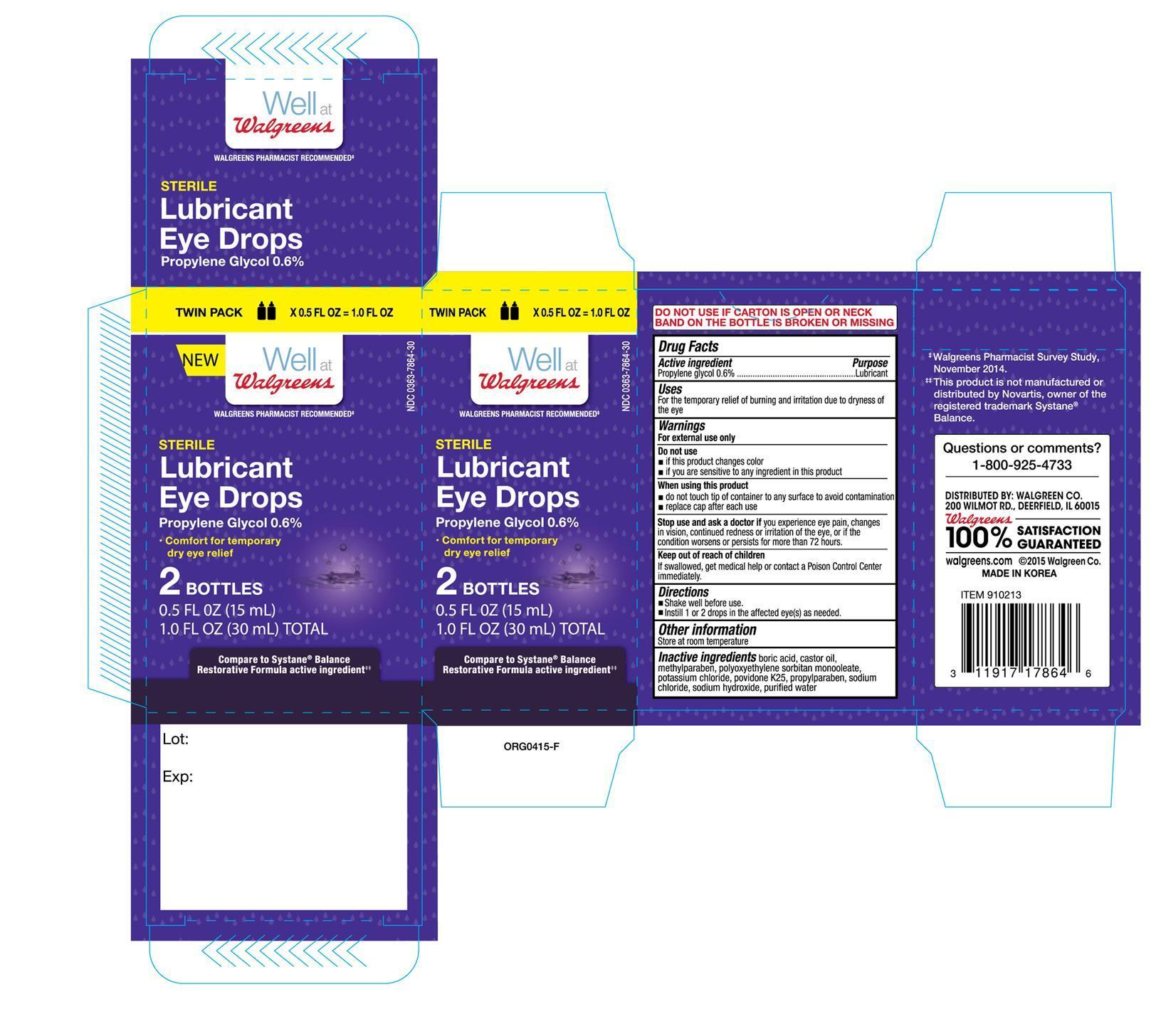 DRUG LABEL: Walgreen Sterile Lubricant
NDC: 0363-7864 | Form: SOLUTION/ DROPS
Manufacturer: Walgreen Company
Category: otc | Type: HUMAN OTC DRUG LABEL
Date: 20150924

ACTIVE INGREDIENTS: PROPYLENE GLYCOL 0.06 mg/1 mL
INACTIVE INGREDIENTS: BORIC ACID; CASTOR OIL; METHYLPARABEN; SORBITAN MONOOLEATE; POTASSIUM CHLORIDE; POVIDONE K25; PROPYLPARABEN; SODIUM CHLORIDE; SODIUM HYDROXIDE; WATER

Active ingredient Purpose

Propylene glycol 0.6%..................................... Lubricant

Uses

- For the temporary relief of burning and irritation due to dryness of the eye

Warnings

For external use only

Do not use

- if this product changes color
- if you are sensitive to any ingredient in this product

When using this product

- do not touch tip of container to any surface to avoid contamination
- replace cap after each use

Stop use and ask a doctor if you experience eye pain, changes in vision, continued redness or irritation of the eye, or if the condition worsens or persists for more than 72 hours

Keep out of reach of children.

If swallowed, get medical help or contact a Poison Control Center immediately.

Directions

- Shake well before use.
- Instill 1 or 2 drops in the affected eye(s) as needed.

Other information

Store at room temperature

Inactive ingredients

boric acid, castor oil, methylparaben, polyoxyethylene sorbitan monooleate, potassium chloride, povidone K25, propylparaben, sodium chloride, sodium hydroxide, purified water

DOSAGE AND ADMINISTRATION

Distributed by:

Walgreen Co.

200 Wilmot Rd.

Deerfield, IL 60015

Made in Korea